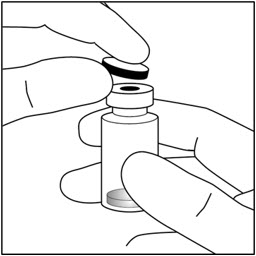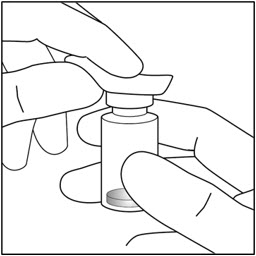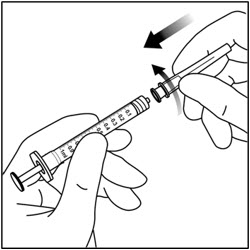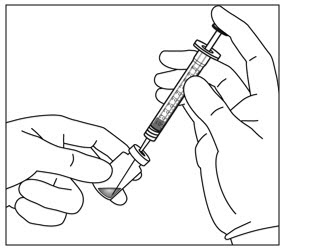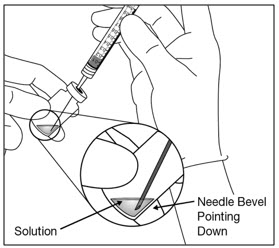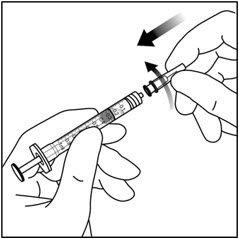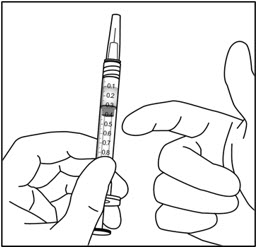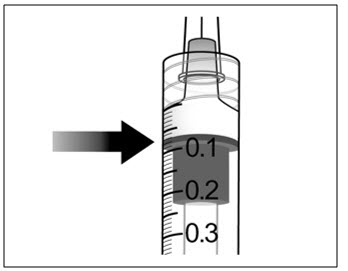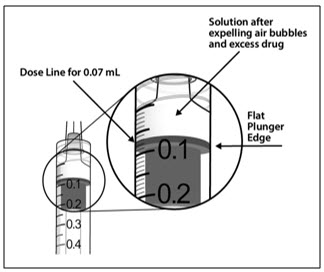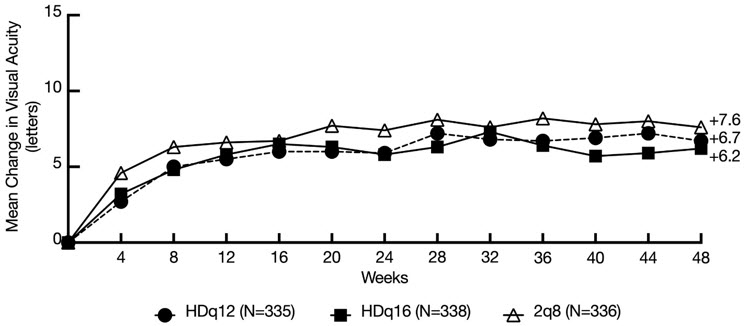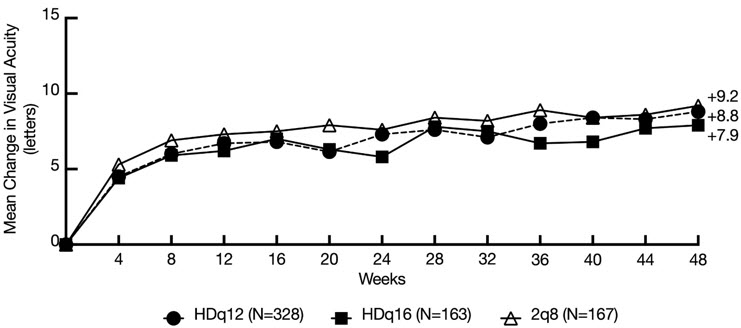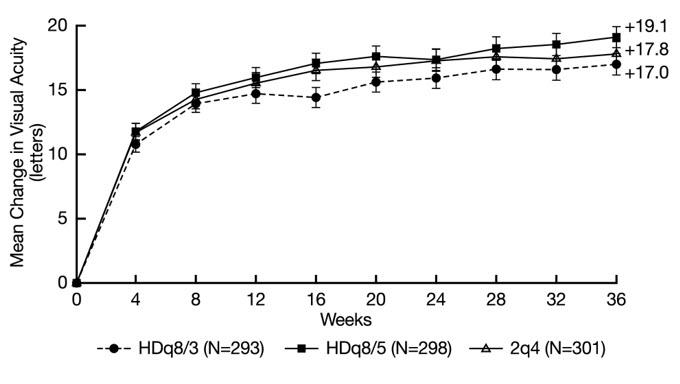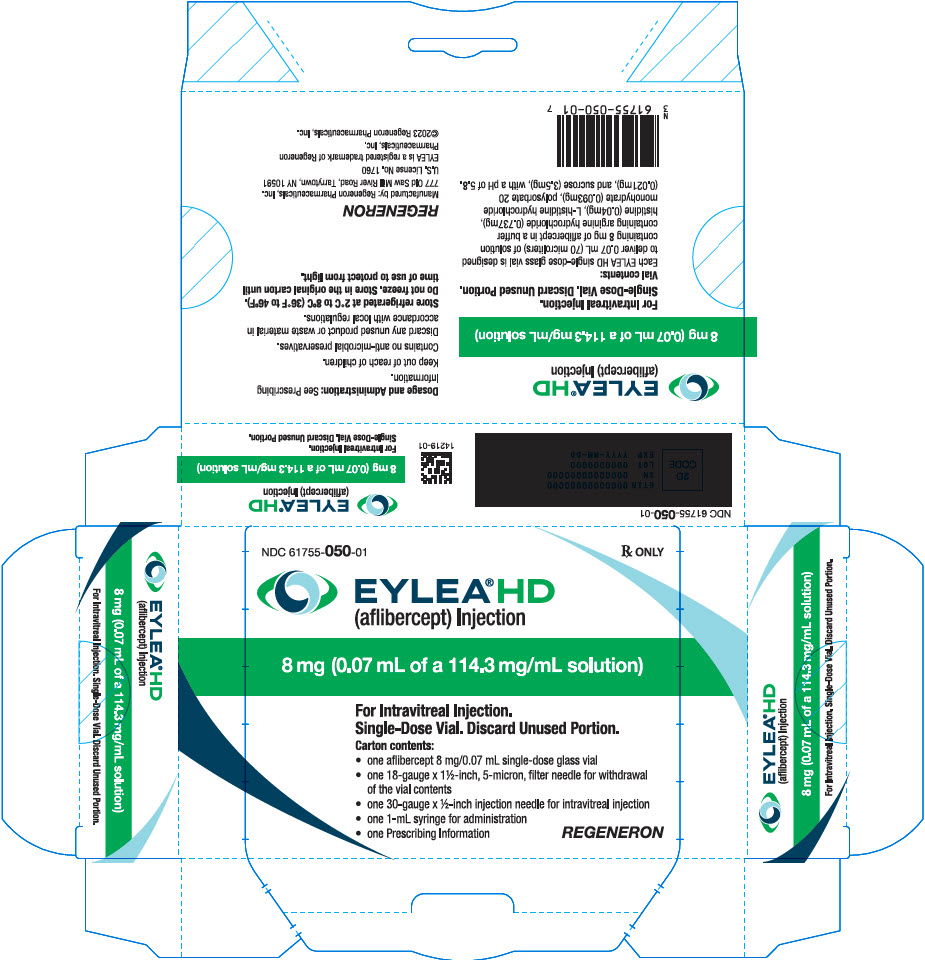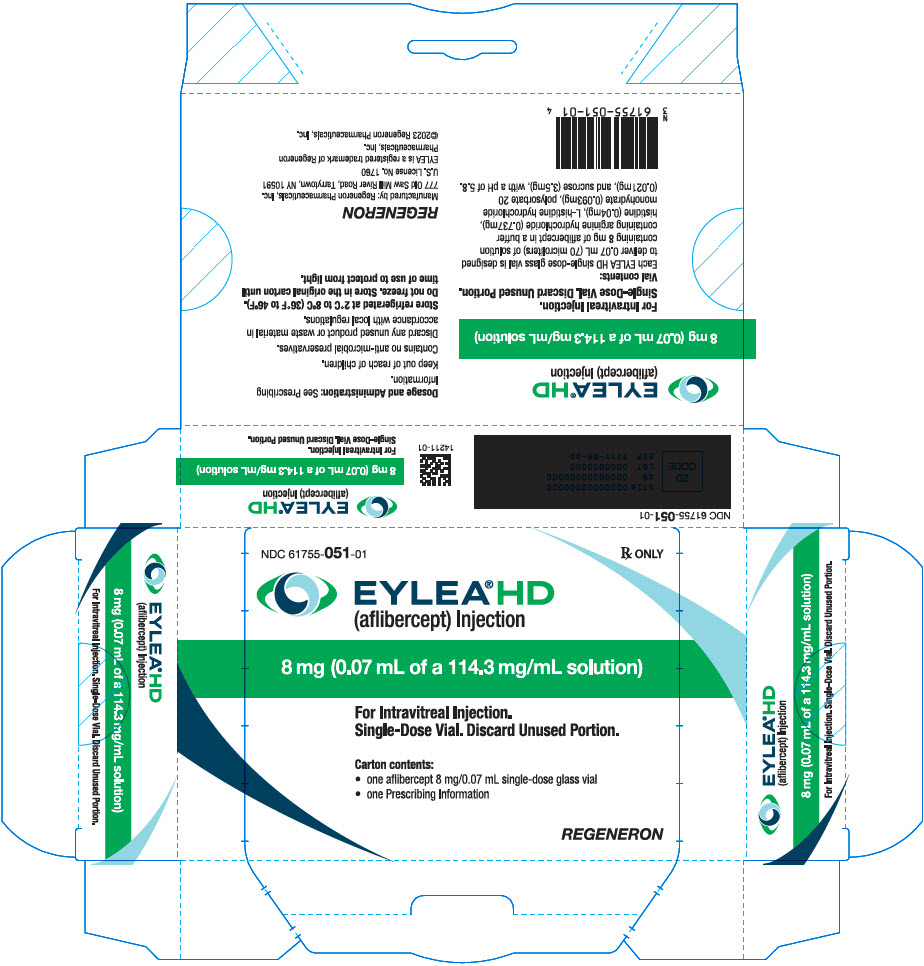 DRUG LABEL: EYLEA HD
NDC: 61755-050 | Form: INJECTION, SOLUTION
Manufacturer: Regeneron Pharmaceuticals, Inc
Category: prescription | Type: HUMAN PRESCRIPTION DRUG LABEL
Date: 20251120

ACTIVE INGREDIENTS: aflibercept 8 mg/0.07 mL
INACTIVE INGREDIENTS: polysorbate 20; sucrose; arginine hydrochloride; histidine; HISTIDINE MONOHYDROCHLORIDE MONOHYDRATE

HIGHLIGHTS OF PRESCRIBING INFORMATION

These highlights do not include all the information needed to use EYLEA HD safely and effectively. See full prescribing information for EYLEA HD.
EYLEA HD® (aflibercept) injection, for intravitreal use
Initial U.S. Approval: 2011

RECENT MAJOR CHANGES

Indications and Usage (1.4) | 11/2025
Dosage and Administration (2.2, 2.3, 2.4, 2.5) | 11/2025
Warnings and Precautions (5.3) | 11/2025

1 INDICATIONS AND USAGE

EYLEA HD is a vascular endothelial growth factor (VEGF) inhibitor indicated for the treatment of patients with:

- Neovascular (Wet) Age-Related Macular Degeneration (nAMD) (1.1)
- Diabetic Macular Edema (DME) (1.2)
- Diabetic Retinopathy (DR) (1.3)
- Macular Edema Following Retinal Vein Occlusion (RVO) (1.4)

2 DOSAGE AND ADMINISTRATION

- Neovascular (Wet) Age-Related Macular Degeneration (nAMD)
  - The recommended dose for EYLEA HD is 8 mg (0.07 mL of 114.3 mg/mL solution) administered by intravitreal injection every 4 weeks (approximately every 28 days +/- 7 days) for the first three doses, followed by 8 mg (0.07 mL of 114.3 mg/mL solution) via intravitreal injection once every 8 to 16 weeks, +/- 1 week. (2.2)
  - Some patients did not maintain a response with extended dosing intervals after successful response to the three initial monthly doses. These patients may benefit from resuming every 4-week dosing (approximately every 28 days +/- 7 days). (2.2)
- Diabetic Macular Edema (DME)
  - The recommended dose for EYLEA HD is 8 mg (0.07 mL of 114.3 mg/mL solution) administered by intravitreal injection every 4 weeks (approximately every 28 days +/- 7 days) for the first three doses, followed by 8 mg (0.07 mL of 114.3 mg/mL solution) via intravitreal injection once every 8 to 16 weeks, +/- 1 week. (2.3)
  - Some patients did not maintain a response with extended dosing intervals after successful response to the three initial monthly doses. These patients may benefit from resuming every 4-week dosing (approximately every 28 days +/- 7 days). (2.3)
- Diabetic Retinopathy (DR)
  - The recommended dose for EYLEA HD is 8 mg (0.07 mL of 114.3 mg/mL solution) administered by intravitreal injection every 4 weeks (approximately every 28 days +/- 7 days) for the first three doses, followed by 8 mg (0.07 mL of 114.3 mg/mL solution) via intravitreal injection once every 8 to 12 weeks, +/- 1 week. (2.4)
  - Some patients did not maintain a response with extended dosing intervals after successful response to the three initial monthly doses. These patients may benefit from resuming every 4-week dosing (approximately every 28 days +/- 7 days). (2.4)
- Macular Edema Following Retinal Vein Occlusion (RVO)
  - The recommended dose for EYLEA HD is 8 mg (0.07 mL of 114.3 mg/mL solution) administered by intravitreal injection every 4 weeks (approximately every 28 days +/- 7 days) for the first three to five doses, followed by 8 mg (0.07 mL of 114.3 mg/mL solution) via intravitreal injection once every 8 weeks, +/- 1 week. (2.5)
  - Some patients did not maintain a response with extended dosing intervals after successful response to the first three to five initial monthly doses. These patients may benefit from resuming every 4-week dosing (approximately every 28 days +/- 7 days). (2.5)

3 DOSAGE FORMS AND STRENGTHS

- Injection: 8 mg (0.07 mL of 114.3 mg/mL solution) in a single-dose vial (3)

4 CONTRAINDICATIONS

- Ocular or periocular infection (4.1)
- Active intraocular inflammation (4.2)
- Hypersensitivity (4.3)

5 WARNINGS AND PRECAUTIONS

- Endophthalmitis, retinal detachments, and retinal vasculitis with or without occlusion may occur following intravitreal injections. Patients should be instructed to report any symptoms suggestive of endophthalmitis, retinal detachment, or retinal vasculitis without delay and should be managed appropriately. (5.1)
- Increases in intraocular pressure have been seen within 60 minutes of an intravitreal injection. (5.2)
- There is a potential risk of arterial thromboembolic events following intravitreal use of VEGF inhibitors. (5.3)

6 ADVERSE REACTIONS

The most common adverse reactions (≥3%) reported in patients treated with EYLEA HD were cataract, conjunctival hemorrhage, corneal epithelium defect, intraocular pressure increased, ocular discomfort/eye pain/eye irritation, retinal hemorrhage, vision blurred, vitreous detachment, and vitreous floaters. (6.1)

To report SUSPECTED ADVERSE REACTIONS, contact Regeneron at 1-855-395-3248 or FDA at 1-800-FDA-1088 or www.fda.gov/medwatch.

FULL PRESCRIBING INFORMATION

1 INDICATIONS AND USAGE

EYLEA HD is indicated for the treatment of:

2 DOSAGE AND ADMINISTRATION

2.1 Important Injection Instructions

For ophthalmic intravitreal injection. EYLEA HD must only be administered by a qualified physician.

A 5-micron sterile filter needle (18-gauge × 1½-inch), a 1-mL Luer lock syringe and a 30-gauge × ½-inch sterile injection needle are needed.

EYLEA HD is available packaged as follows:

- Vial Only
- Vial Kit with Injection Components (filter needle, syringe, injection needle)

[see How Supplied/Storage and Handling (16)].

2.2 Neovascular (Wet) Age-Related Macular Degeneration (nAMD)

The recommended dose for EYLEA HD is 8 mg (0.07 mL of 114.3 mg/mL solution) administered by intravitreal injection every 4 weeks (approximately every 28 days +/- 7 days) for the first three doses, followed by 8 mg (0.07 mL of 114.3 mg/mL solution) via intravitreal injection once every 8 to 16 weeks, +/- 1 week.

Some patients did not maintain a response with extended dosing intervals after successful response to the three initial monthly doses [see Clinical Studies (14.1)]. These patients may benefit from resuming every 4-week dosing (approximately every 28 days +/- 7 days).

2.3 Diabetic Macular Edema (DME)

The recommended dose for EYLEA HD is 8 mg (0.07 mL of 114.3 mg/mL solution) administered by intravitreal injection every 4 weeks (approximately every 28 days +/- 7 days) for the first three doses, followed by 8 mg (0.07 mL of 114.3 mg/mL solution) via intravitreal injection once every 8 to 16 weeks, +/- 1 week.

Some patients did not maintain a response with extended dosing intervals after successful response to the three initial monthly doses [see Clinical Studies (14.2)]. These patients may benefit from resuming every 4-week dosing (approximately every 28 days +/- 7 days).

2.4 Diabetic Retinopathy (DR)

The recommended dose for EYLEA HD is 8 mg (0.07 mL of 114.3 mg/mL solution) administered by intravitreal injection every 4 weeks (approximately every 28 days +/- 7 days) for the first three doses, followed by 8 mg (0.07 mL of 114.3 mg/mL solution) via intravitreal injection once every 8 to 12 weeks, +/- 1 week.

Some patients did not maintain a response with extended dosing intervals after successful response to the three initial monthly doses [see Clinical Studies (14.3)]. These patients may benefit from resuming every 4-week dosing (approximately every 28 days +/- 7 days).

2.5 Macular Edema Following Retinal Vein Occlusion (RVO)

The recommended dose for EYLEA HD is 8 mg (0.07 mL of 114.3 mg/mL solution) administered by intravitreal injection every 4 weeks (approximately every 28 days +/- 7 days) for the first three to five doses, followed by 8 mg (0.07 mL of 114.3 mg/mL solution) via intravitreal injection once every 8 weeks, +/- 1 week.

Some patients did not maintain a response with extended dosing intervals after successful response to the first three to five initial monthly doses [see Clinical Studies (14.4)]. These patients may benefit from resuming every 4-week dosing (approximately every 28 days +/- 7 days).

2.6 Preparation for Administration

The EYLEA HD glass vial is for one-time use in one eye only. Discard unused portion. EYLEA HD does not contain an anti-microbial preservative. Extraction of multiple doses from a single vial may increase the risk of contamination and subsequent infection.

Do not use if the package or its components are expired, damaged, or have been tampered with.

Check the label on the vial to make sure you have the correct aflibercept strength.

Prepare for intravitreal injection with the following medical devices for single use.

- a 5-micron sterile filter needle (18-gauge × 1½-inch)
- a 1-mL sterile Luer lock syringe (with marking to measure 0.07 mL)
- a sterile injection needle (30-gauge × ½-inch)

1. Parenteral drug products should be inspected visually for particulate matter and discoloration prior to administration, whenever solution and container permit. Do not use the vial if particulates, cloudiness, or discoloration are visible.
2. Remove the protective plastic cap from the vial (see Figure 1).

Figure 1:

3. Clean the top of the vial with an alcohol wipe (see Figure 2).

Figure 2:

4. Use aseptic technique to carry out steps 4 – 11. Remove the 18-gauge × 1½-inch, 5-micron, filter needle and the 1-mL syringe from their packaging. Attach the filter needle to the syringe by twisting it onto the Luer lock syringe tip (see Figure 3).

Figure 3:

5. Push the filter needle into the center of the vial stopper until the needle is completely inserted into the vial and the tip touches the bottom or bottom edge of the vial.
6. Withdraw all of the EYLEA HD vial contents into the syringe, keeping the vial in an upright position, slightly inclined to ease complete withdrawal. To deter the introduction of air, ensure the bevel of the filter needle is submerged into the liquid. Continue to tilt the vial during withdrawal keeping the bevel of the filter needle submerged in the liquid (see Figure 4a and Figure 4b).

Figure 4a:

Figure 4b:

7. Ensure that the plunger rod is drawn sufficiently back when emptying the vial in order to completely empty the filter needle.
8. Remove the filter needle from the syringe and properly dispose of the filter needle. Note: Filter needle is not to be used for intravitreal injection.
9. Remove the 30-gauge × ½-inch injection needle from its packaging and attach the injection needle to the syringe by firmly twisting the injection needle onto the Luer lock syringe tip (see Figure 5).

Figure 5:

10. Holding the syringe with the needle pointing up, check the syringe for bubbles. If there are bubbles, gently tap the syringe with your finger until the bubbles rise to the top (see Figure 6).

Figure 6:

11. To eliminate all of the bubbles and to expel excess drug, SLOWLY depress the plunger so that the plunger tip aligns with the line that marks 0.07 mL on the syringe (see Figure 7a and Figure 7b).

Figure 7a:

Figure 7b:

2.7 Injection Procedure

The intravitreal injection procedure should be carried out under controlled aseptic conditions, which include surgical hand disinfection and the use of sterile gloves, a sterile drape, and a sterile eyelid speculum (or equivalent). Adequate anesthesia and a topical broad–spectrum microbicide should be given prior to the injection.

Immediately following the intravitreal injection, patients should be monitored for elevation in intraocular pressure. Appropriate monitoring may consist of a check for perfusion of the optic nerve head or tonometry. If required, a sterile paracentesis needle should be available.

Following intravitreal injection, patients and/or caregivers should be instructed to report any signs and/or symptoms suggestive of endophthalmitis or retinal detachment (e.g., eye pain, redness of the eye, photophobia, blurring of vision) without delay [see Patient Counseling Information (17)].

Each vial should only be used for the treatment of a single eye. If the contralateral eye requires treatment, a new vial should be used and the sterile field (including a new syringe, gloves, drapes, eyelid speculum, filter and injection needles) should be changed before EYLEA HD is administered to the other eye.

After injection, discard any unused product or waste material in accordance with local regulations.

3 DOSAGE FORMS AND STRENGTHS

EYLEA HD is a clear to slightly opalescent, colorless to pale yellow solution available as:

- Injection: 8 mg (0.07 mL of a 114.3 mg/mL solution) in a single-dose glass vial

4 CONTRAINDICATIONS

4.1 Ocular or Periocular Infections

EYLEA HD is contraindicated in patients with ocular or periocular infections.

4.2 Active Intraocular Inflammation

EYLEA HD is contraindicated in patients with active intraocular inflammation.

4.3 Hypersensitivity

EYLEA HD is contraindicated in patients with known hypersensitivity to aflibercept or any of the excipients in EYLEA HD. Hypersensitivity reactions may manifest as rash, pruritus, urticaria, severe anaphylactic/anaphylactoid reactions, or severe intraocular inflammation.

5 WARNINGS AND PRECAUTIONS

5.1 Endophthalmitis, Retinal Detachments, and Retinal Vasculitis with or without Occlusion

Intravitreal injections including those with aflibercept have been associated with endophthalmitis and retinal detachments [see Adverse Reactions (6.1)] and, more rarely, retinal vasculitis with or without occlusion [see Adverse Reactions (6.2)]. Proper aseptic injection technique must always be used when administering EYLEA HD. Patients and/or caregivers should be instructed to report any signs and/or symptoms suggestive of endophthalmitis, retinal detachment, or retinal vasculitis without delay and should be managed appropriately [see Dosage and Administration (2.7) and Patient Counseling Information (17)].

5.2 Increase in Intraocular Pressure

Acute increases in intraocular pressure have been seen within 60 minutes of intravitreal injection, including with EYLEA HD [see Adverse Reactions (6.1)]. Sustained increases in intraocular pressure have also been reported after repeated intravitreal dosing with vascular endothelial growth factor (VEGF) inhibitors. Intraocular pressure and the perfusion of the optic nerve head should be monitored and managed appropriately [see Dosage and Administration (2.7)].

5.3 Thromboembolic Events

There is a potential risk of arterial thromboembolic events (ATEs) following intravitreal use of VEGF inhibitors, including EYLEA HD. ATEs are defined as nonfatal stroke, nonfatal myocardial infarction, or vascular death (including deaths of unknown cause). The incidence of reported thromboembolic events in the wet AMD study (PULSAR) from baseline through week 48 was 0.4% (3 out of 673) in the combined group of patients treated with EYLEA HD compared with 1.5% (5 out of 336) in patients treated with EYLEA 2 mg. The incidence of reported thromboembolic events in the DME study (PHOTON) from baseline to week 48 was 3.1% (15 out of 491) in the combined group of patients treated with EYLEA HD compared with 3.6% (6 out of 167) in patients treated with EYLEA 2 mg. The incidence of reported thromboembolic events in the RVO study (QUASAR) from baseline to week 36 was 0.5% (3 out of 591) in the combined group of patients treated with EYLEA HD compared with 1.7% (5 out of 301) in patients treated with EYLEA 2 mg.

6 ADVERSE REACTIONS

The following potentially serious adverse reactions are described elsewhere in the labeling:

- Hypersensitivity [see Contraindications (4.3)]
- Endophthalmitis, Retinal Detachments, and Retinal Vasculitis with or without Occlusion [see Warnings and Precautions (5.1)]
- Increase in intraocular pressure [see Warnings and Precautions (5.2)]
- Thromboembolic events [see Warnings and Precautions (5.3)]

6.1 Clinical Trials Experience

Because clinical trials are conducted under widely varying conditions, adverse reaction rates observed in the clinical trials of a drug cannot be directly compared to rates in other clinical trials of the same or another drug and may not reflect the rates observed in practice.

A total of 1755 patients were treated with EYLEA HD and 804 patients were treated with EYLEA 2 mg in three clinical studies. The most common adverse reactions reported in ≥3% of patients treated with EYLEA HD were cataract, conjunctival hemorrhage, corneal epithelium defect, intraocular pressure increased, ocular discomfort/eye pain/eye irritation, retinal hemorrhage, vision blurred, vitreous detachment and vitreous floaters.

Neovascular (Wet) Age-Related Macular Degeneration (AMD) and Diabetic Macular Edema (DME)

The data described below reflect exposure to EYLEA HD administered every 12 weeks (HDq12), EYLEA HD administered every 16 weeks (HDq16), or EYLEA 2 mg administered every 8 weeks (2q8) in controlled clinical studies (PULSAR and PHOTON), each for 48 weeks [see Clinical Studies (14.1, 14.2)].

Table 1: Adverse Reactions (≥1%) in at least one group in the PULSAR or PHOTON studies
Adverse Reactions | PULSAR |  |  | PHOTON
Adverse Reactions | EYLEA HDq12 | EYLEA HDq16 | EYLEA 2q8 | EYLEA HDq12 | EYLEA HDq16 | EYLEA 2q8
 | n=335 | n=338 | n=336 | n=328 | n=163 | n=167
Cataract [Represents grouping of related terms] | 4% | 4% | 4% | 3% | 6% | 3%
Conjunctival hemorrhage | 3% | 2% | 1% | 4% | 4% | 4%
Intraocular pressure increased | 4% | 4% | 2% | 3% | 1% | 4%
Ocular discomfort/eye pain/eye irritation | 3% | 3% | 2% | 4% | 2% | 4%
Vision blurred | 4% | 6% | 7% | 3% | 3% | 4%
Vitreous floaters | 1% | 4% | 3% | 5% | 2% | 3%
Vitreous detachment | 2% | 3% | 2% | 4% | 2% | 1%
Corneal epithelium defect | 2% | 2% | 3% | 3% | 6% | 1%
Retinal hemorrhage | 3% | 3% | 4% | 0 | 4% | 1%
Intraocular inflammation | 1% | 1% | 1% | 1% | 0 | 1%
Retinal pigment epithelial tear/epitheliopathy | 2% | 1% | 2% | <1% | 0 | 0
Vitreous hemorrhage | <1% | 1% | 1% | 2% | 1% | 1%
Retinal Detachment | 1% | <1% | 0 | <1% | 1% | 0
Foreign body sensation in eyes | 1% | 1% | 2% | <1% | 0 | 0
Retinal pigment epithelial detachment | 1% | 1% | 2% | 0 | 0 | 0

Adverse drug reactions (ADRs) reported in <1% of participants treated with EYLEA HD were ocular hyperemia (includes adverse events of conjunctival hyperemia, conjunctival irritation, ocular hyperemia), lacrimation increased, eyelid edema, hypersensitivity (includes adverse events of rash, urticaria, pruritus), retinal tear and injection site hemorrhage.

Macular Edema Following Retinal Vein Occlusion (RVO)

The data described below reflects 36 weeks exposure to EYLEA HD administered every 8 weeks (HDq8) after 3 or 5 initial monthly doses (HDq4), or EYLEA 2 mg administered every 4 weeks (2q4) in a controlled clinical study (QUASAR). [see Clinical Studies (14.4)].

Table 2: Most Common Adverse Reactions (≥1%) in at least one group in the QUASAR study
Adverse Reactions | EYLEA HDq8 following 3 initial doses (HDq4) (N=293) | EYLEA HDq8 following 5 initial doses (HDq4) (N=298) | EYLEA 2q4 (N=301)
Intraocular pressure increased [Represents grouping of related terms] | 7% | 6% | 3%
Vision blurred | 5% | 3% | 2%
Conjunctival hemorrhage | 3% | 2% | 2%
Ocular discomfort/eye pain/eye irritation | 3% | 3% | 1%
Vitreous detachment | 3% | 3% | 1%
Cataract | 2% | 4% | 3%
Corneal epithelium defect | 2% | 2% | 2%
Dry eye | 2% | 2% | 2%
Vitreous floaters | 1% | 1% | 1%
Intraocular inflammation | 1% | <1% | 1%
Vitreous hemorrhage | 1% | 1% | 0
Hypersensitivity [Represents reported non-ocular adverse events of hypersensitivity, rash, urticaria and pruritus] | 1% | 1% | 1%

Adverse reactions reported in <1% of the patients treated with EYLEA HD in the RVO study were foreign body sensation in eyes (includes foreign body sensation in eyes and sensation of foreign body), ocular hyperaemia (includes conjunctival hyperemia, conjunctival irritation, ocular hyperemia), retinal hemorrhage, retinal pigment epithelial detachment (includes detachment of retinal pigment epithelium), retinal pigment epithelial tear/epitheliopathy (includes retinal pigment epitheliopathy), and retinal tear.

6.2 Postmarketing Experience

The following adverse reactions have been identified during postapproval use of aflibercept. Because these reactions are reported voluntarily from a population of uncertain size, it is not always possible to reliably estimate their frequency or establish a causal relationship to drug exposure.

Eye disorders:

- Retinal vasculitis and occlusive retinal vasculitis related to intravitreal injection with aflibercept (reported at a rate of 0.6 and 0.2 per 1 million injections, respectively, based on postmarketing experience from November 2011 until November 2023).
- Scleritis.

8 USE IN SPECIFIC POPULATIONS

8.1 Pregnancy

Risk Summary

Adequate and well-controlled studies with EYLEA HD have not been conducted in pregnant women. Aflibercept produced adverse embryofetal effects in rabbits, including external, visceral, and skeletal malformations. A fetal No Observed Adverse Effect Level (NOAEL) was not identified. At the lowest dose shown to produce adverse embryofetal effects, systemic exposure (based on AUC for free aflibercept) was approximately 0.9 -fold of the population pharmacokinetic estimated exposure in humans after an intravitreal dose of 8 mg (see Data).

Animal reproduction studies are not always predictive of human response, and it is not known whether EYLEA HD can cause fetal harm when administered to a pregnant woman. Based on the anti-VEGF mechanism of action for aflibercept [see Clinical Pharmacology (12.1)], treatment with EYLEA HD may pose a risk to human embryofetal development. EYLEA HD should be used during pregnancy only if the potential benefit justifies the potential risk to the fetus.

All pregnancies have a background risk of birth defect, loss, or other adverse outcomes. The background risk of major birth defects and miscarriage for the indicated population is unknown. In the U.S. general population, the estimated background risk of major birth defects and miscarriage in clinically recognized pregnancies is 2-4% and 15-20%, respectively.

Data

Animal Data

In two embryofetal development studies, aflibercept produced adverse embryofetal effects when administered every three days during organogenesis to pregnant rabbits at intravenous doses ≥3 mg per kg, or every six days during organogenesis at subcutaneous doses ≥0.1 mg per kg.

Adverse embryofetal effects included increased incidences of postimplantation loss and fetal malformations, including anasarca, umbilical hernia, diaphragmatic hernia, gastroschisis, cleft palate, ectrodactyly, intestinal atresia, spina bifida, encephalomeningocele, heart and major vessel defects, and skeletal malformations (fused vertebrae, sternebrae, and ribs; supernumerary vertebral arches and ribs; and incomplete ossification). The maternal No Observed Adverse Effect Level (NOAEL) in these studies was 3 mg per kg. Aflibercept produced fetal malformations at all doses assessed in rabbits and the fetal NOAEL was not identified. At the lowest dose shown to produce adverse embryofetal effects in rabbits (0.1 mg per kg), systemic exposure (AUC) of free aflibercept was approximately 0.9-fold of the population pharmacokinetic estimated systemic exposure (AUC) in humans after an intravitreal dose of 8 mg.

8.2 Lactation

Risk Summary

There is no information regarding the presence of aflibercept in human milk, the effects of the drug on the breastfed infant, or the effects of the drug on milk production/excretion. Because many drugs are excreted in human milk, and because the potential for absorption and harm to infant growth and development exists, EYLEA HD is not recommended during breastfeeding.

The developmental and health benefits of breastfeeding should be considered along with the mother's clinical need for EYLEA HD and any potential adverse effects on the breastfed child from EYLEA HD.

8.3 Females and Males of Reproductive Potential

Contraception

Females of reproductive potential are advised to use effective contraception prior to the initial dose, during treatment, and for at least 4 months after the last intravitreal injection of EYLEA HD.

Infertility

There are no data regarding the effects of EYLEA HD on human fertility. Aflibercept adversely affected female and male reproductive systems in cynomolgus monkeys when administered by intravenous injection at a dose 91 times higher (based on AUC of free aflibercept) than the corresponding systemic level estimated based on population pharmacokinetic analysis in humans following an intravitreal dose of 8 mg. A No Observed Adverse Effect Level (NOAEL) was not identified. These findings were reversible within 20 weeks after cessation of treatment [see Nonclinical Toxicology (13.1)].

8.4 Pediatric Use

The safety and effectiveness of EYLEA HD in pediatric patients have not been established.

8.5 Geriatric Use

In the clinical studies, approximately 66% (1156/1755) of the patients in the HD groups were 65 years of age or older and approximately 31% (543/1755) of the patients were 75 years of age or older.

No overall differences in safety or effectiveness of EYLEA HD have been observed.

10 OVERDOSAGE

Overdosing with increased injection volume may increase intraocular pressure. Therefore, in case of overdosage, intraocular pressure should be monitored and if deemed necessary by the treating physician, adequate treatment should be initiated.

11 DESCRIPTION

Aflibercept is a recombinant fusion protein consisting of portions of human VEGF receptors 1 and 2 extracellular domains fused to the Fc portion of human IgG1 formulated as an iso-osmotic solution for intravitreal administration. Aflibercept is a dimeric glycoprotein and contains glycosylation, constituting an additional 15% of the total molecular mass, resulting in a total molecular weight of 115 kDa. Aflibercept is produced in recombinant Chinese hamster ovary (CHO) cells.

EYLEA HD (aflibercept) injection is a sterile, clear to slightly opalescent, and colorless to pale yellow solution. EYLEA HD is supplied as a sterile, aqueous solution for intravitreal injection in a single-dose glass vial designed to deliver 0.07 mL (70 microliters) of solution containing 8 mg of aflibercept in a buffer containing arginine hydrochloride (0.737 mg), histidine (0.04 mg), L-histidine hydrochloride monohydrate (0.093 mg), polysorbate 20 (0.021 mg), sucrose (3.5 mg) and water for injection with a pH of 5.8. EYLEA HD does not contain an anti-microbial preservative.

12 CLINICAL PHARMACOLOGY

12.1 Mechanism of Action

Vascular endothelial growth factor-A (VEGF-A) and placental growth factor (PlGF) are members of the VEGF family of angiogenic factors that can act as mitogenic, chemotactic, and vascular permeability factors for endothelial cells. VEGF acts via two receptor tyrosine kinases, VEGFR-1 and VEGFR-2, present on the surface of endothelial cells. PlGF binds only to VEGFR-1, which is also present on the surface of leucocytes. Activation of these receptors by VEGF-A can result in neovascularization and vascular permeability.

Aflibercept acts as a soluble decoy receptor that binds VEGF-A and PlGF, and thereby can inhibit the binding and activation of these cognate VEGF receptors.

12.2 Pharmacodynamics

Increased retinal thickness, assessed by optical coherence tomography (OCT), is associated with nAMD, DME, and RVO. Reductions in central subfield thickness (CST) were observed across all treatment arms throughout the three Phase 3 studies in nAMD, DME, and RVO.

12.3 Pharmacokinetics

EYLEA HD is administered intravitreally to exert local effects in the eye. In patients with wet AMD, or DME, following intravitreal administration of EYLEA HD, a fraction of the administered dose is expected to bind with endogenous VEGF in the eye to form an inactive aflibercept: VEGF complex. Once absorbed into the systemic circulation, aflibercept presents in the plasma as free aflibercept (unbound to VEGF) and a more predominant stable inactive form with circulating endogenous VEGF (i.e., aflibercept: VEGF complex).

Absorption/Distribution

As no relevant differences in pharmacokinetics between the nAMD, DME, and RVO populations were observed based on a population pharmacokinetic analysis of the data, population pharmacokinetic estimated parameters are presented for the combined populations. Following unilateral intravitreal administration of 8 mg aflibercept, the mean (SD) Cmax of free aflibercept in plasma was 0.32 (0.27) mg/L, and the median time to maximal concentration in plasma was 2.9 days. The accumulation of free aflibercept in plasma following three initial monthly intravitreal doses was minimal (mean accumulation ratio 1.2); subsequently, no further accumulation was observed.

The volume of distribution of free aflibercept following intravenous (I.V.) administration of aflibercept is approximately 7 L.

Metabolism/Elimination

Aflibercept is a therapeutic protein and no drug metabolism studies have been conducted. Aflibercept is expected to undergo elimination through both target-mediated disposition via binding to free endogenous VEGF and metabolism via proteolysis. The median time to reach non-quantifiable concentrations of free aflibercept in plasma for 8 mg administered intravitreally was 3.5 weeks.

Specific Populations

Renal and Hepatic Impairment

Population pharmacokinetic analysis revealed that systemic exposures to aflibercept in patients with mild to severe renal impairment (eGFR 15 to < 90 mL/min, estimated using the Chronic Kidney Disease Epidemiology Collaboration (CKD-EPI) equation for eGFR were similar to those with normal renal function. Mild hepatic impairment had no influence on systemic exposures to aflibercept compared to patients with normal hepatic function. No data for patients with moderate and severe hepatic impairment are available. No dose adjustment based on renal or hepatic impairment status is needed.

Other

No dosage adjustment is required for any of the populations that have been studied (e.g., age and race).

12.6 Immunogenicity

The observed incidence of anti-drug antibodies is highly dependent on the sensitivity and specificity of the assay. Differences in assay methods preclude meaningful comparisons of the incidence of anti-drug antibodies in the studies described below with the incidence of anti-drug antibodies for other products.

During the 48-week treatment with aflibercept administrated IVT, the incidence of anti-aflibercept antibody formation in the 8 mg treatment groups was 2.7% (25/937 participants with nAMD [PULSAR] or DME [PHOTON]).

13 NONCLINICAL TOXICOLOGY

13.1 Carcinogenesis, Mutagenesis, Impairment of Fertility

No studies have been conducted on the mutagenic or carcinogenic potential of aflibercept. Effects on male and female fertility were assessed as part of a 6-month study in monkeys with intravenous administration of aflibercept at weekly doses ranging from 3 to 30 mg per kg. Absent or irregular menses associated with alterations in female reproductive hormone levels and changes in sperm morphology and motility were observed at all dose levels. In addition, females showed decreased ovarian and uterine weight accompanied by compromised luteal development and reduction of maturing follicles. These changes correlated with uterine and vaginal atrophy. All changes were reversible within 20 weeks after cessation of treatment. A No Observed Adverse Effect Level (NOAEL) was not identified. Intravenous administration of the lowest dose of aflibercept assessed in monkeys (3 mg per kg) resulted in systemic exposure (AUC) for free aflibercept that was 91 times higher than the population pharmacokinetic estimated systemic exposure in humans after an intravitreal dose of 8 mg.

13.2 Animal Toxicology and/or Pharmacology

Erosions and ulcerations of the respiratory epithelium in nasal turbinates in monkeys treated with aflibercept intravitreally were observed at intravitreal doses of 2, 4 or 7 mg per eye. At the NOAEL of 0.5 mg per eye in monkeys, the systemic exposure (AUC) for free aflibercept was approximately 3 times higher than the population pharmacokinetic estimated exposure observed in humans after an intravitreal dose of 8 mg. Similar effects were not seen in clinical studies [see Clinical Studies (14)].

14 CLINICAL STUDIES

14.1 Neovascular (Wet) Age-Related Macular Degeneration (nAMD)

The safety and efficacy of EYLEA HD were assessed in a randomized, multi-center, double-masked, active-controlled study (PULSAR) in treatment-naïve patients with nAMD. A total of 1009 patients were treated and analyzed for efficacy (673 with EYLEA HD). Patients were randomly assigned in a 1:1:1 ratio to 1 of 3 treatment groups: 1) EYLEA HD administered every 12 weeks following 3 initial monthly doses (HDq12); 2) EYLEA HD administered every 16 weeks following 3 initial monthly doses (HDq16); 3) EYLEA 2 mg administered every 8 weeks (2q8) following 3 initial monthly doses. In the EYLEA HD groups, patients could be treated as frequently as every 8 weeks based on protocol-defined visual and anatomic criteria, starting at week 16. Patients ranged from 50 to 96 years of age with a mean of 74.5 years. At baseline, mean visual acuity was approximately 60 letters (range: 24 to 78 letters).

The primary efficacy endpoint was the change from baseline in BCVA at week 48 as measured by the Early Treatment Diabetic Retinopathy Study (ETDRS) letter score.

Both HDq12 and HDq16 treatments were shown to be non-inferior and clinically equivalent to 2q8 treatment with respect to the change in BCVA score at week 48 using the pre-specified non-inferiority margin of 4 letters. 6.2% of total EYLEA HD treated patients who met protocol-defined criteria to be treated every 8 weeks did not maintain a response with every 8 weeks dosing after successful response to the 3 initial monthly doses. In patients completing week 48, the mean number of injections administered were 5.2 in the HDq16 group (n=312), 6.1 in the HDq12 group (n=316) and 6.9 in the EYLEA q8 group (n=309). Detailed results from the analysis of the PULSAR study are shown in Table 3 and Figure 8 below.

Efficacy results in all subgroups (e.g., age, gender, geographic region, ethnicity, race, baseline BCVA and lesion type) were consistent with those in the overall population.

Table 3: Efficacy Outcomes (Full Analysis Set) in PULSAR Study
Efficacy Outcomes | EYLEA HDq12 | EYLEA HDq16 | EYLEA 2q8
Full Analysis Set [Full Analysis Set (FAS) includes all randomized patients who received at least 1 dose of study medication] | N=335 | N=338 | N=336
Mean change in BCVA as measured by ETDRS letter score from baseline (SD) at week 48 [Observed values at week 48: n=299 for HDq12; n=289 for HDq16; n=285 for 2q8] | 6.7 (12.6) | 6.2 (11.7) | 7.6 (12.2)
LS mean (SE) change from baseline [Estimate based on the MMRM model, was computed for the differences of HDq12 minus 2q8 and HDq16 minus 2q8, respectively, with two-sided 95% CIs] | 6.1 (0.8) | 5.9 (0.7) | 7.0 (0.7)
Difference in LS mean (95% CI) | -1.0 (-2.9, 0.9) | -1.1 (-3.0, 0.7)
BCVA = Best Corrected Visual Acuity; ETDRS = Early Treatment Diabetic Retinopathy Study; SD = Standard Deviation; LS = Least Square; SE = Standard Error; CI = Confidence Interval; MMRM = Mixed Model for Repeated Measurements

Figure 8: Mean Change from Baseline in BCVA as measured by ETDRS Letter Score by Visits through Week 48 (Observed Cases)

14.2 Diabetic Macular Edema (DME)

The safety and efficacy of EYLEA HD was assessed in a randomized, multi-center, double-masked, active-controlled study (PHOTON) in patients with DME involving the center of the macula. A total of 658 patients were treated and analyzed for efficacy (491 with EYLEA HD). Patients were randomly assigned in a 2:1:1 ratio to 1 of 3 treatment groups: 1) EYLEA HD administered every 12 weeks following 3 initial monthly doses (HDq12); 2) EYLEA HD administered every 16 weeks following 3 initial monthly doses (HDq16); 3) EYLEA 2 mg administered every 8 weeks (2q8) following 5 initial monthly doses. In the EYLEA HD groups, patients could be treated as frequently as every 8 weeks based on protocol-defined visual and anatomic criteria, starting at week 16. Patient ages ranged from 24 to 90 years with a mean of 62.3 years. A total of 44% of patients were previously treated for DME. At baseline, the overall mean visual acuity was 63 letters (range: 24 to 79 letters).

The primary efficacy endpoint was the change from baseline in BCVA at week 48 as measured by the ETDRS letter score. Both HDq12 and HDq16 treatments were shown to be non-inferior and clinically equivalent to 2q8 treatment with respect to the change in BCVA score at week 48 using the pre-specified non-inferiority margin of 4 letters. 1.5% of total EYLEA HD treated patients who met protocol-defined criteria to be treated every 8 weeks did not maintain a response with every 8 weeks dosing after successful response to the 3 initial monthly doses. In patients completing week 48, the mean number of injections administered were 5.0 in the HDq16 group (n=155), 6.0 in the HDq12 group (n=300) and 7.9 in the EYLEA q8 group (n=157). Detailed results from the analysis of the PHOTON study are shown in Table 4 and Figure 9 below.

Table 4: Efficacy Outcomes (Full Analysis Set) in PHOTON Study
Efficacy Outcomes | EYLEA HDq12 | EYLEA HDq16 | EYLEA 2q8
Full Analysis Set [FAS includes all randomized patients who received at least 1 dose of study medication] | N=328 | N=163 | N=167
Mean change in BCVA as measured by ETDRS letter score from baseline (SD) at week 48 [Observed values at week 48: n=277 for HDq12; n=149 for HDq16; n=150 for 2q8] | 8.8 (9.0) | 7.9 (8.4) | 9.2 (9.0)
LS mean (SE) change from baseline [Estimate based on the MMRM model, was computed for the differences of HDq12 minus 2q8 and HDq16 minus 2q8, respectively with two-sided 95% CIs] | 8.1 (0.6) | 7.2 (0.7) | 8.7 (0.7)
Difference in LS mean (95% CI) | -0.6 (-2.3, 1.1) | -1.4 (-3.3, 0.4)
BCVA = Best Corrected Visual Acuity; ETDRS = Early Treatment Diabetic Retinopathy Study; SD = Standard Deviation; LS = Least Square; SE = Standard Error; CI = Confidence Interval; MMRM = Mixed Model for Repeated Measurements.

Efficacy results in all subgroups (e.g., age, gender, geographic region, ethnicity, race, baseline, BCVA, baseline CRT and prior DME treatment) were consistent with those in the overall population.

Figure 9: Mean Change from Baseline in BCVA as measured by ETDRS Letter Score by Visits through Week 48 (Observed Cases)

14.3 Diabetic Retinopathy (DR)

Efficacy and safety data of EYLEA HD in diabetic retinopathy (DR) are derived from the PHOTON study.

In the PHOTON study, a key efficacy outcome was the change in the Early Treatment Diabetic Retinopathy Study (ETDRS) Diabetic Retinopathy Severity Scale (ETDRS-DRSS). Each EYLEA HD group was compared to the 2q8 group using a NI margin of 10%.

The ETDRS-DRSS score was assessed at baseline and approximately every 3 months thereafter for the duration of the study [see Clinical Studies (14.2)]. Baseline ETDRS-DRSS scores were generally balanced across treatment groups. 1.5% of total EYLEA HD treated patients who met protocol-defined criteria to be treated every 8 weeks did not maintain a response with every 8 weeks dosing after successful response to the 3 initial monthly doses.

Results from the analysis of ETDRS-DRSS scores at week 48 in the PHOTON study are shown in Table 5 below:

Table 5: Proportion of Patients Who Achieved a ≥2-Step Improvement from Baseline in the ETDRS-DRSS Score at Week 48 (Full Analysis Set) in PHOTON
Efficacy Outcomes | EYLEA HDq12 | EYLEA HDq16 | EYLEA 2q8
Full Analysis Set [FAS includes all randomized patients who received at least 1 dose of study medication] | N=328 | N=163 | N=167
Proportion of patients with a ≥2-step improvement on ETDRS-DRSS from Baseline (%) [Last observation carried forward] | 29% | 20% | 27%
Difference [Difference with confidence interval (CI) was calculated using Mantel-Haenszel weighting scheme] (%) (95% CI) | 2% (-6.6, 10.6) | -8% (-16.9, 1.8)
Missing or non-gradable post-baseline ETDRS-DRSS values were imputed using the last gradable ETDRS-DRSS values. Patients were considered as non-responders if all post-baseline measurements were missing or non-gradable. Missing or ungradable baseline was not included in the denominator.

The EYLEA HDq16 did not meet the non-inferiority criteria for the proportion of patients with a ≥2-step improvement on ETDRS-DRSS and is not considered clinically equivalent to EYLEA administered every 8 weeks.

Results of the subgroups (e.g., age, gender, race, ethnicity, baseline BCVA and prior DME treatment) on the proportion of patients who achieved a ≥2-step improvement on the ETDRS-DRSS from baseline to week 48 were, in general, consistent with those in the overall population.

14.4 Macular Edema Following Retinal Vein Occlusion (RVO)

The safety and efficacy of EYLEA HD was assessed in a randomized, multi-center, double-masked, active-controlled study (QUASAR) in patients with treatment naïve macular edema secondary to RVO. A total of 892 patients (425 with CRVO/HRVO and 467 with BRVO) were treated and analyzed for efficacy (591 with EYLEA HD). Patients were randomly assigned in a 1:1:1 ratio to 1 of 3 treatment groups: 1) EYLEA HD administered every 8 weeks, following 3 initial monthly doses (HDq8/3); 2) EYLEA HD administered every 8 weeks, following 5 initial monthly doses (HDq8/5); 3) EYLEA 2 mg administered every 4 weeks (2q4). Dosing intervals could be shortened or extended by 4-week increments based on protocol-defined visual and anatomic criteria. Intervals could be shortened beginning at week 16 for the HDq8/3 group, at week 24 for the HDq8/5 group and, if previously extended, at week 40 for the 2q4 group; intervals could be extended beginning at week 32 for the HDq8/3 and 2q4 groups and at week 40 for the HDq8/5 group. Patient ages ranged from 23 to 95 years with a mean of 65.9 years. At baseline, mean visual acuity was approximately 55 letters (range: 18 to 74 letters).

The primary efficacy endpoint was the change from baseline in BCVA at week 36 as measured by the Early Treatment Diabetic Retinopathy Study (ETDRS) letter score.

Both EYLEA HD groups were shown to be non-inferior and clinically equivalent to EYLEA with respect to the change in BCVA score at week 36 using the pre-specified non-inferiority margin of 4 letters. 9.1% of total EYLEA HD treated patients met protocol-defined criteria to be treated every 4 weeks. Detailed results from the analysis of the QUASAR study are shown in Table 6 and Figure 10 below.

Efficacy results in all subgroups (e.g., age, gender, geographic region, ethnicity, race, baseline BCVA and RVO subtype) were generally consistent with those in the overall population.

Table 6: Efficacy Outcomes (Full Analysis Set) in QUASAR Study
Efficacy Outcomes | EYLEA HDq8/3 | EYLEA HDq8/5 | EYLEA 2q4
Full Analysis Set [Full Analysis Set (FAS) includes all randomized patients who received at least 1 dose of study medication] | N=293 | N=298 | N=301
Mean change in BCVA as measured by ETDRS letter score from baseline (SD) at week 36 [Observed values at week 36: n=260 for HDq8/3; n=248 for HDq8/5; n=264 for 2q4] | 17.0 (11.8) | 19.1 (11.2) | 17.8 (13.1)
LS mean (SE) change from baseline [Estimate based on the MMRM model, was computed for the differences of HDq8/3 minus 2q4 and HDq8/5 minus 2q4, respectively, with two-sided 95% CIs] | 17.0 (0.7) | 17.9 (0.6) | 17.1 (0.7)
Difference in LS mean (95% CI) | -0.1 (-2.0, 1.9) | 0.8 (-1.1, 2.7)
BCVA = Best Corrected Visual Acuity; ETDRS = Early Treatment Diabetic Retinopathy Study; SD = Standard Deviation; LS = Least Square; SE = Standard Error; CI = Confidence Interval; MMRM = Mixed Model for Repeated Measurements

Figure 10: Mean Change from Baseline in BCVA as measured by ETDRS Letter Score by Visits through Week 36 (Observed Cases)

16 HOW SUPPLIED/STORAGE AND HANDLING

16.1 How Supplied

EYLEA HD (aflibercept) is a clear to slightly opalescent, colorless to pale yellow solution supplied in the following presentations [see Dosage and Administration (2.6) and (2.7)]. Each vial is for single eye use only. Discard unused portion.

NDC NUMBER | CARTON TYPE | CARTON CONTENTS
61755-050-01 | Vial Kit with Injection Components | - one EYLEA HD 8 mg (0.07 mL of a 114.3 mg/mL solution), single-dose glass vial - one 18-gauge × 1½-inch, 5-micron, filter needle for withdrawal of the vial contents - one 30-gauge × ½-inch injection needle for intravitreal injection - one 1-mL syringe for administration - one Prescribing Information
61755-051-01 | Vial Only | - one EYLEA HD 8 mg (0.07 mL of a 114.3 mg/mL solution) single-dose glass vial - one Prescribing Information

16.2 Storage and Handling

Refrigerate EYLEA HD at 2°C to 8°C (36°F to 46°F). Do not freeze. Do not use beyond the date stamped on the carton and container label. Store in the original carton until time of use to protect from light.

17 PATIENT COUNSELING INFORMATION

In the days following EYLEA HD administration, patients are at risk of developing endophthalmitis, retinal detachment, or retinal vasculitis with or without occlusion. If the eye becomes red, sensitive to light, painful, or develops a change in vision, advise patients and/or caregivers to seek immediate care from an ophthalmologist [see Warnings and Precautions (5.1)].

Patients may experience temporary visual disturbances after an intravitreal injection with EYLEA HD and the associated eye examinations [see Adverse Reactions (6.1)]. Advise patients not to drive or use machinery until visual function has recovered sufficiently.

Manufactured by:

Regeneron Pharmaceuticals, Inc.

777 Old Saw Mill River Road

Tarrytown, NY 10591-6707

U.S. License Number 1760

For patent information: https://www.regeneron.com/downloads/us-patent-products.pdf

EYLEA HD is a registered trademark of Regeneron Pharmaceuticals, Inc.

©2025, Regeneron Pharmaceuticals, Inc.

All rights reserved.

Date: November 2025

PRINCIPAL DISPLAY PANEL - 0.07 mL Vial Carton - 050

NDC 61755-050-01

Rx ONLY

EYLEA®HD
(aflibercept) Injection

8 mg (0.07 mL of a 114.3 mg/mL solution)

For Intravitreal Injection.
Single-Dose Vial. Discard Unused Portion.

Carton contents:

- one aflibercept 8 mg/0.07 mL single-dose glass vial
- one 18-gauge × 1½-inch, 5-micron, filter needle for withdrawal
  of the vial contents
- one 30-gauge × ½-inch injection needle for intravitreal injection
- one 1-mL syringe for administration
- one Prescribing Information

REGENERON

PRINCIPAL DISPLAY PANEL - 0.07 mL Vial Carton - 051

NDC 61755-051-01

Rx ONLY

EYLEA®HD
(aflibercept) Injection

8 mg (0.07 mL of a 114.3 mg/mL solution)

For Intravitreal Injection.
Single-Dose Vial. Discard Unused Portion.

Carton contents:

- one aflibercept 8 mg/0.07 mL single-dose glass vial
- one Prescribing Information

REGENERON